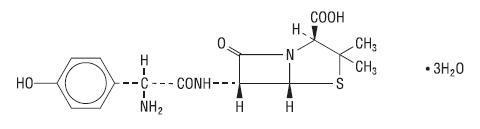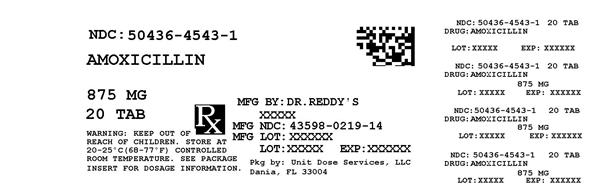 DRUG LABEL: AMOXICILLIN
NDC: 50436-4543 | Form: TABLET, FILM COATED
Manufacturer: Unit Dose Services
Category: prescription | Type: HUMAN PRESCRIPTION DRUG LABEL
Date: 20170701

ACTIVE INGREDIENTS: AMOXICILLIN 875 mg/1 1
INACTIVE INGREDIENTS: SILICON DIOXIDE; CROSPOVIDONE, UNSPECIFIED; D&C RED NO. 30; HYPROMELLOSE 2910 (5 MPA.S); MAGNESIUM STEARATE; MICROCRYSTALLINE CELLULOSE; POLYETHYLENE GLYCOL, UNSPECIFIED; SODIUM STARCH GLYCOLATE TYPE A POTATO; TITANIUM DIOXIDE

HIGHLIGHTS OF PRESCRIBING INFORMATION

These highlights do not include all the information needed to use AMOXICILLIN safely and effectively. See full prescribing information for AMOXICILLIN.
AMOXICILLIN capsules, tablets, and powder for oral suspension
Initial U.S. Approval: 1974

RECENT MAJOR CHANGES

Indications and Usage, Gonorrhea (1.5)..................................................... Removed 9/2015
Dosage and Administration, Gonorrhea (2.1) ..............................................Removed 9/2015

1 INDICATIONS AND USAGE

AMOXICILLIN is a penicillin-class antibacterial indicated for treatment of infections due to susceptible strains of designated microorganisms.

- Infections of the ear, nose, throat, genitourinary tract, skin and skin structure, and lower respiratory tract. (1.1 – 1.4)
- In combination for treatment of H. pylori infection and duodenal ulcer disease. (1.5)

To reduce the development of drug-resistant bacteria and maintain the effectiveness of AMOXICILLIN and other antibacterial drugs, AMOXICILLIN should be used only to treat infections that are proven or strongly suspected to be caused by bacteria. (1.6)

2 DOSAGE AND ADMINISTRATION

- In adults, 750-1750 mg/day in divided doses every 8-12 hours. In Pediatric Patients > 3 Months of Age, 20-45 mg/kg/day in divided doses every 8-12 hours. Refer to full prescribing information for specific dosing regimens. (2.1, 2.2 , 2.3)
- The upper dose for neonates and infants ≤ 3 months is 30 mg/kg/day divided every 12 hours. (2.2)
- Dosing for H. pylori Infection: Triple therapy: 1 gram AMOXICILLIN, 500 mg clarithromycin, and 30 mg lansoprazole, all given twice daily (every 12 hours) for 14 days. Dual therapy: 1 gram AMOXICILLIN and 30 mg lansoprazole, each given three times daily (every 8 hours) for 14 days. (2.3)
- Reduce the dose in patients with severe renal impairment (GFR < 30 mL/min). (2.4)

3 DOSAGE FORMS AND STRENGTHS

- Capsules: 250 mg, 500 mg (3)
- Tablets: 500 mg, 875 mg (3)
- Powder for Oral Suspension: 125 mg/5 mL, 200 mg/5 mL, 250 mg/5 mL, 400 mg/5 mL (3)

4 CONTRAINDICATIONS

- History of a serious hypersensitivity reaction (e.g., anaphylaxis or Stevens-Johnson syndrome) to amoxicillin or to other beta-lactams (e.g., penicillins or cephalosporins) (4)

5 WARNINGS AND PRECAUTIONS

- Anaphylactic reactions: Serious and occasionally fatal anaphylactic reactions have been reported in patients on penicillin therapy. Serious anaphylactic reactions require immediate emergency treatment with supportive measures. (5.1)
- Clostridium difficile-associated diarrhea (ranging from mild diarrhea to fatal colitis): Evaluate if diarrhea occurs. (5.2)

6 ADVERSE REACTIONS

The most common adverse reactions (> 1%) observed in clinical trials of AMOXICILLIN capsules, tablets or oral suspension were diarrhea, rash, vomiting, and nausea. (6.1)

To report SUSPECTED ADVERSE REACTIONS, contact Dr. Reddy’s Laboratories Inc., at 1-888-375-3784 or FDA at 1-800-FDA-1088 or www.fda.gov/medwatch.

7 DRUG INTERACTIONS

- Probenicid decreases renal tubular secretion of amoxicillin which may result in increased blood levels of amoxicillin. (7.1)
- Concomitant use of Amoxicillin and oral anticoagulants may increase the prolongation of prothrombin time. (7.2)
- Coadministration with allopurinol increases the risk of rash. (7.3)
- Amoxicillin may reduce the efficacy of oral contraceptives. (7.4)

8 USE IN SPECIFIC POPULATIONS

- Pediatric: Modify dose in patients 12 weeks or younger (≤ 3 months). (8.4)

FULL PRESCRIBING INFORMATION

1 INDICATIONS AND USAGE

1.1 Infections of the Ear, Nose, and Throat

AMOXICILLIN is indicated in the treatment of infections due to susceptible (ONLY β-lactamase–negative) isolates of Streptococcus species. (α and β hemolytic isolates only), Streptococcus pneumoniae, Staphylococcus spp., or Haemophilus influenzae.

1.2 Infections of the Genitourinary Tract

AMOXICILLIN is indicated in the treatment of infections due to susceptible (ONLY β-lactamase–negative) isolates of Escherichia coli, Proteus mirabilis, or Enterococcus faecalis.

1.3 Infections of the Skin and Skin Structure

AMOXICILLIN is indicated in the treatment of infections due to susceptible (ONLY β-lactamase–negative) isolates of Streptococcus spp. (α- and β-hemolytic isolates only), Staphylococcus spp., or E. coli.

1.4 Infections of the Lower Respiratory Tract

AMOXICILLIN is indicated in the treatment of infections due to susceptible (ONLY β-lactamase–negative) isolates of Streptococcus spp. (α- and β-hemolytic isolates only), S. pneumoniae, Staphylococcus spp., or H. influenzae.

1.5 Helicobacter pylori Infection

Triple therapy for Helicobacter pylori with clarithromycin and lansoprazole:
AMOXICILLIN, in combination with clarithromycin plus lansoprazole as triple therapy, is indicated for the treatment of patients with H. pylori infection and duodenal ulcer disease (active or 1 year history of a duodenal ulcer) to eradicate H. pylori. Eradication of H. pylori has been shown to reduce the risk of duodenal ulcer recurrence.

Dual therapy for H. pylori with lansoprazole: AMOXICILLIN, in combination with lansoprazole delayed release capsules as dual therapy, is indicated for the treatment of patients with H. pylori infection and duodenal ulcer disease (active or 1 year history of a duodenal ulcer) who are either allergic or intolerant to clarithromycin or in whom resistance to clarithromycin is known or suspected. (See the clarithromycin package insert, MICROBIOLOGY.) Eradication of H. pylori has been shown to reduce the risk of duodenal ulcer recurrence.

1.6 Usage

To reduce the development of drug resistant bacteria and maintain the effectiveness of AMOXICILLIN and other antibacterial drugs, AMOXICILLIN should be used only to treat infections that are proven or strongly suspected to be caused by bacteria. When culture and susceptibility information are available, they should be considered in selecting or modifying antibacterial therapy. In the absence of such data, local epidemiology and susceptibility patterns may contribute to the empiric selection of therapy.

2 DOSAGE AND ADMINISTRATION

2.1 Dosing for Adult and Pediatric Patients > 3 Months of Age

Treatment should be continued for a minimum of 48 to 72 hours beyond the time that the patient becomes asymptomatic or evidence of bacterial eradication has been obtained. It is recommended that there be at least 10 days’ treatment for any infection caused by Streptococcus pyogenes to prevent the occurrence of acute rheumatic fever. In some infections, therapy may be required for several weeks. It may be necessary to continue clinical and/or bacteriological follow-up for several months after cessation of therapy.

Table 1. Dosing Recommendations for Adult and Pediatric Patients > 3 Months of Age
Infection | Severitya | Usual Adult Dose | Usual Dose for Children > 3 Monthsb
Ear/Nose/Throat Skin/Skin Structure Genitourinary Tract | Mild/Moderate | 500 mg every 12 hours or 250 mg every 8 hours | 25 mg/kg/day in divided doses every 12 hours or 20 mg/kg/day in divided doses every 8 hours
 | Severe | 875 mg every 12 hours or 500 mg every 8 hours | 45 mg/kg/day in divided doses every 12 hours or 40 mg/kg/day in divided doses every 8 hours
Lower Respiratory Tract | Mild/Moderate or Severe | 875 mg every 12 hours or 500 mg every 8 hours | 45 mg/kg/day in divided doses every 12 hours or 40 mg/kg/day in divided doses every 8 hours

a Dosing for infections caused by bacteria that are intermediate in their susceptibility to amoxicillin should follow the recommendations for severe infections.
b The children’s dosage is intended for individuals whose weight is less than 40 kg. Children weighing 40 kg or more should be dosed according to the adult recommendations.

2.2 Dosing in Neonates and Infants Aged ≤ 12 Weeks (≤ 3 Months)

Treatment should be continued for a minimum of 48 to 72 hours beyond the time that the patient becomes asymptomatic or evidence of bacterial eradication has been obtained. It is recommended that there be at least 10 days’ treatment for any infection caused by Streptococcus pyogenes to prevent the occurrence of acute rheumatic fever. Due to incompletely developed renal function affecting elimination of amoxicillin in this age group, the recommended upper dose of AMOXICILLIN is 30 mg/kg/day divided every 12 hours. There are currently no dosing recommendations for pediatric patients with impaired renal function.

2.3 Dosing for H. pylori Infection

Triple therapy: The recommended adult oral dose is 1 gram AMOXICILLIN, 500 mg clarithromycin, and 30 mg lansoprazole, all given twice daily (every 12 hours) for 14 days.

Dual therapy: The recommended adult oral dose is 1 gram AMOXICILLIN and 30 mg lansoprazole, each given three times daily (every 8 hours) for 14 days.

Please refer to clarithromycin and lansoprazole full prescribing information.

2.4 Dosing in Renal Impairment

- Patients with impaired renal function do not generally require a reduction in dose unless the impairment is severe.
- Severely impaired patients with a glomerular filtration rate of < 30 mL/min. should not receive a 875-mg dose.
- Patients with a glomerular filtration rate of 10 to 30 mL/min should receive 500 mg or 250 mg every 12 hours, depending on the severity of the infection.
- Patients with a glomerular filtration rate less than 10 mL/min should receive 500 mg or 250 mg every 24 hours, depending on severity of the infection.
- Hemodialysis patients should receive 500 mg or 250 mg every 24 hours, depending on severity of the infection. They should receive an additional dose both during and at the end of dialysis.

2.5 Directions for Mixing Oral Suspension

Tap bottle until all powder flows freely. Add approximately 1/3 of the total amount of water for reconstitution (see Table 2) and shake vigorously to wet powder. Add remainder of the water and again shake vigorously.

Table 2. Amount of Water for Mixing Oral Suspension
Strength | Bottle Size | Amount of Water Required for Reconstitution
Oral Suspension 125 mg/5 mL | 80 mL | 62 mL
 | 100 mL | 78 mL
 | 150 mL | 116 mL
Oral Suspension 200 mg/5 mL | 50 mL | 39 mL
 | 75 mL | 57 mL
 | 100 mL | 76 mL
Oral Suspension 250 mg/5 mL | 80 mL | 59 mL
 | 100 mL | 74 mL
 | 150 mL | 111 mL
Oral Suspension 400 mg/5 mL | 50 mL | 36 mL
 | 75 mL | 54 mL
 | 100 mL | 71 mL

After reconstitution, the required amount of suspension should be placed directly on the child’s tongue for swallowing. Alternate means of administration are to add the required amount of suspension to formula, milk, fruit juice, water, ginger ale, or cold drinks. These preparations should then be taken immediately.

NOTE: SHAKE ORAL SUSPENSION WELL BEFORE USING. Keep bottle tightly closed. Any unused portion of the reconstituted suspension must be discarded after 14 days. Refrigeration is preferable, but not required.

3 DOSAGE FORMS AND STRENGTHS

Capsules: 250 mg, 500 mg. Each capsule of AMOXICILLIN, with royal blue opaque cap and pink opaque body, contains 250 mg or 500 mg amoxicillin as the trihydrate. The cap and body of the 250-mg capsule are imprinted with the product name AMOXIL and 250; the cap and body of the 500-mg capsule are imprinted with AMOXIL and 500.

Tablets: 500 mg, 875 mg. Each tablet contains 500 mg or 875 mg amoxicillin as the trihydrate. Each film-coated, capsule-shaped, pink tablet is debossed with AMOXIL centered over 500 or 875, respectively. The 875-mg tablet is scored on the reverse side.

Powder for Oral Suspension: 125 mg/5 mL, 200 mg/5 mL, 250 mg/5 mL, 400 mg/5 mL. Each 5 mL of reconstituted strawberry-flavored suspension contains 125 mg amoxicillin as the trihydrate. Each 5 mL of reconstituted bubble-gum-flavored suspension contains 200 mg, 250 mg or 400 mg amoxicillin as the trihydrate.

4 CONTRAINDICATIONS

AMOXICILLIN is contraindicated in patients who have experienced a serious hypersensitivity reaction (e.g., anaphylaxis or Stevens-Johnson syndrome) to AMOXICILLIN or to other β-lactam antibiotics (e.g., penicillins and cephalosporins).

5 WARNINGS AND PRECAUTIONS

5.1 Anaphylactic Reactions

Serious and occasionally fatal hypersensitivity (anaphylactic) reactions have been reported in patients on penicillin therapy including amoxicillin. Although anaphylaxis is more frequent following parenteral therapy, it has occurred in patients on oral penicillins. These reactions are more likely to occur in individuals with a history of penicillin hypersensitivity and/or a history of sensitivity to multiple allergens. There have been reports of individuals with a history of penicillin hypersensitivity who have experienced severe reactions when treated with cephalosporins. Before initiating therapy with AMOXICILLIN, careful inquiry should be made regarding previous hypersensitivity reactions to penicillins, cephalosporins, or other allergens. If an allergic reaction occurs, AMOXICILLIN should be discontinued and appropriate therapy instituted.

5.2 Clostridium difficile Associated Diarrhea

Clostridium difficile associated diarrhea (CDAD) has been reported with use of nearly all antibacterial agents, including AMOXICILLIN, and may range in severity from mild diarrhea to fatal colitis. Treatment with antibacterial agents alters the normal flora of the colon leading to overgrowth of C. difficile.

C. difficile produces toxins A and B which contribute to the development of CDAD. Hypertoxin-producing strains of C. difficile cause increased morbidity and mortality, as these infections can be refractory to antimicrobial therapy and may require colectomy. CDAD must be considered in all patients who present with diarrhea following antibacterial use. Careful medical history is necessary since CDAD has been reported to occur over 2 months after the administration of antibacterial agents.

If CDAD is suspected or confirmed, ongoing antibiotic use not directed against C. difficile may need to be discontinued. Appropriate fluid and electrolyte management, protein supplementation, antibiotic treatment of C. difficile, and surgical evaluation should be instituted as clinically indicated.

5.3 Development of Drug-Resistant Bacteria

Prescribing AMOXICILLIN either in the absence of a proven or strongly suspected bacterial infection is unlikely to provide benefit to the patient, and increases the risk of the development of drug-resistant bacteria.

5.4 Use in Patients With Mononucleosis

A high percentage of patients with mononucleosis who receive amoxicillin develop an erythematous skin rash. Thus, amoxicillin should not be administered to patients with mononucleosis.

5.5 Phenylketonurics

Amoxicillin chewable tablets contain aspartame which contains phenylalanine. Each 200 mg chewable tablet contains 1.82 mg phenylalanine; each 400 mg chewable tablet contains 3.64 mg phenylalanine. The oral suspensions of Amoxicillin do not contain phenylalanine and can be used by phenylketonurics.

6 ADVERSE REACTIONS

The following are discussed in more detail in other sections of the labeling:

- Anaphylactic reactions [see Warnings and Precautions (5.1)]
- CDAD [see Warnings and Precautions (5.2)]

6.1 Clinical Trials Experience

Because clinical trials are conducted under widely varying conditions, adverse reaction rates observed in the clinical trials of a drug cannot be directly compared to rates in the clinical trials of another drug and may not reflect the rates observed in practice.

The most common adverse reactions (> 1%) observed in clinical trials of AMOXICILLIN capsules, tablets or oral suspension were diarrhea, rash, vomiting, and nausea.

Triple therapy: The most frequently reported adverse events for patients who received triple therapy (amoxicillin/clarithromycin/ lansoprazole) were diarrhea (7%), headache (6%), and taste perversion (5%).

Dual therapy: The most frequently reported adverse events for patients who received double therapy amoxicillin/lansoprazole were diarrhea (8%) and headache (7%). For more information on adverse reactions with clarithromycin or lansoprazole, refer to the Adverse Reactions section of their package inserts.

6.2 Postmarketing or Other Experience

In addition to adverse events reported from clinical trials, the following events have been identified during postmarketing use of penicillins. Because they are reported voluntarily from a population of unknown size, estimates of frequency cannot be made. These events have been chosen for inclusion due to a combination of their seriousness, frequency of reporting, or potential causal connection to AMOXICILLIN.

- Infections and Infestations: Mucocutaneous candidiasis.
- Gastrointestinal: Black hairy tongue, and hemorrhagic/pseudomembranous colitis.
  Onset of pseudomembranous colitis symptoms may occur during or after antibacterial treatment [see Warnings and Precautions (5.2)].
- Hypersensitivity Reactions: Anaphylaxis [see Warnings and Precautions (5.1)]. Serum sickness–like reactions, erythematous maculopapular rashes, erythema multiforme, Stevens-Johnson syndrome, exfoliative dermatitis, toxic epidermal necrolysis, acute generalized exanthematous pustulosis, hypersensitivity vasculitis, and urticaria have been reported.
- Liver: A moderate rise in AST and/or ALT has been noted, but the significance of this finding is unknown. Hepatic dysfunction including cholestatic jaundice, hepatic cholestasis and acute cytolytic hepatitis have been reported.
- Renal: Crystalluria has been reported [see Overdosage (10)].
- Hemic and Lymphatic Systems: Anemia, including hemolytic anemia, thrombocytopenia, thrombocytopenic purpura, eosinophilia, leukopenia, and agranulocytosis have been reported. These reactions are usually reversible on discontinuation of therapy and are believed to be hypersensitivity phenomena.
- Central Nervous System: Reversible hyperactivity, agitation, anxiety, insomnia, confusion, convulsions, behavioral changes, and/or dizziness have been reported.
- Miscellaneous: Tooth discoloration (brown, yellow, or gray staining) has been reported. Most reports occurred in pediatric patients. Discoloration was reduced or eliminated with brushing or dental cleaning in most cases.

7 DRUG INTERACTIONS

7.1 Probenecid

Probenecid decreases the renal tubular secretion of amoxicillin. Concurrent use of amoxicillin and probenecid may result in increased and prolonged blood levels of amoxicillin.

7.2 Oral Anticoagulants

Abnormal prolongation of prothrombin time (increased international normalized ratio [INR]) has been reported in patients receiving amoxicillin and oral anticoagulants. Appropriate monitoring should be undertaken when anticoagulants are prescribed concurrently. Adjustments in the dose of oral anticoagulants may be necessary to maintain the desired level of anticoagulation.

7.3 Allopurinol

The concurrent administration of allopurinol and amoxicillin increases the incidence of rashes in patients receiving both drugs as compared to patients receiving amoxicillin alone. It is not known whether this potentiation of amoxicillin rashes is due to allopurinol or the hyperuricemia present in these patients.

7.4 Oral Contraceptives

AMOXICILLIN may affect the gut flora, leading to lower estrogen reabsorption and reduced efficacy of combined oral estrogen/progesterone contraceptives.

7.5 Other Antibacterials

Chloramphenicol, macrolides, sulfonamides, and tetracyclines may interfere with the bactericidal effects of penicillin. This has been demonstrated in vitro; however, the clinical significance of this interaction is not well documented.

7.6 Effects on Laboratory Tests

High urine concentrations of ampicillin may result in false-positive reactions when testing for the presence of glucose in urine using CLINITEST®, Benedict’s Solution, or Fehling’s Solution. Since this effect may also occur with amoxicillin, it is recommended that glucose tests based on enzymatic glucose oxidase reactions (such as CLINISTIX®) be used.

Following administration of ampicillin or amoxicillin to pregnant women, a transient decrease in plasma concentration of total conjugated estriol, estriol-glucuronide, conjugated estrone, and estradiol has been noted.

8 USE IN SPECIFIC POPULATIONS

8.1 Pregnancy

TERATOGENIC EFFECTS

Teratogenic Effects: Pregnancy Category B. Reproduction studies have been performed in mice and rats at doses up to 2000 mg/kg (3 and 6 times the 3 g human dose, based on body surface area). There was no evidence of harm to the fetus due to amoxicillin. There are, however, no adequate and well-controlled studies in pregnant women. Because animal reproduction studies are not always predictive of human response, amoxicillin should be used during pregnancy only if clearly needed.

8.2 Labor and Delivery

Oral ampicillin is poorly absorbed during labor. It is not known whether use of amoxicillin in humans during labor or delivery has immediate or delayed adverse effects on the fetus, prolongs the duration of labor, or increases the likelihood of the necessity for an obstetrical intervention.

8.3 Nursing Mothers

Penicillins have been shown to be excreted in human milk. Amoxicillin use by nursing mothers may lead to sensitization of infants. Caution should be exercised when amoxicillin is administered to a nursing woman.

8.4 Pediatric Use

Because of incompletely developed renal function in neonates and young infants, the elimination of amoxicillin may be delayed. Dosing of AMOXICILLIN should be modified in pediatric patients 12 weeks or younger (≤ 3 months). [See Dosage and Administration (2.2).]

8.5 Geriatric Use

An analysis of clinical studies of AMOXICILLIN was conducted to determine whether subjects aged 65 and over respond differently from younger subjects. These analyses have not identified differences in responses between the elderly and younger patients, but a greater sensitivity of some older individuals cannot be ruled out.

This drug is known to be substantially excreted by the kidney, and the risk of toxic reactions to this drug may be greater in patients with impaired renal function. Because elderly patients are more likely to have decreased renal function, care should be taken in dose selection, and it may be useful to monitor renal function.

8.6 Dosing in Renal Impairment

Amoxicillin is primarily eliminated by the kidney and dosage adjustment is usually required in patients with severe renal impairment (GFR < 30 mL/min). See Dosing in Renal Impairment (2.4) for specific recommendations in patients with renal impairment.

10 OVERDOSAGE

In case of overdosage, discontinue medication, treat symptomatically, and institute supportive measures as required. A prospective study of 51 pediatric patients at a poison-control center suggested that overdosages of less than 250 mg/kg of amoxicillin are not associated with significant clinical symptoms.

Interstitial nephritis resulting in oliguric renal failure has been reported in a small number of patients after overdosage with amoxicillin^1.

Crystalluria, in some cases leading to renal failure, has also been reported after amoxicillin overdosage in adult and pediatric patients. In case of overdosage, adequate fluid intake and diuresis should be maintained to reduce the risk of amoxicillin crystalluria.

Renal impairment appears to be reversible with cessation of drug administration. High blood levels may occur more readily in patients with impaired renal function because of decreased renal clearance of amoxicillin. Amoxicillin may be removed from circulation by hemodialysis.

11 DESCRIPTION

Formulations of AMOXICILLIN contain amoxicillin, a semisynthetic antibiotic, an analog of ampicillin, with a broad spectrum of bactericidal activity against many Gram-positive and Gram-negative microorganisms. Chemically, it is (2S,5R,6R)-6-[(R)-(-)-2-amino-2-(p-hydroxyphenyl)acetamido]-3,3-dimethyl-7-oxo-4-thia-1-azabicyclo [3.2.0]heptane-2-carboxylic acid trihydrate. It may be represented structurally as:

The amoxicillin molecular formula is C16H19N3O5S•3H2O, and the molecular weight is 419.45.

Capsules: Each capsule of AMOXICILLIN, with royal blue opaque cap and pink opaque body, contains 250 mg or 500 mg amoxicillin as the trihydrate. The cap and body of the 250-mg capsule are imprinted with the product name AMOXIL and 250; the cap and body of the 500-mg capsule are imprinted with AMOXIL and 500. Inactive ingredients: D&C Red No. 28, FD&C Blue No. 1, FD&C Red No. 40, gelatin, magnesium stearate, and titanium dioxide.

Tablets: Each tablet contains 500 mg or 875 mg amoxicillin as the trihydrate. Each film-coated, capsule-shaped, pink tablet is debossed with AMOXIL centered over 500 or 875, respectively. The 875-mg tablet is scored on the reverse side. Inactive ingredients: Colloidal silicon dioxide, crospovidone, D&C Red No. 30 aluminum lake, hypromellose, magnesium stearate, microcrystalline cellulose, polyethylene glycol, sodium starch glycolate, and titanium dioxide.

Powder for Oral Suspension: Each 5 mL of reconstituted suspension contains 125 mg, 200 mg, 250 mg or 400 mg amoxicillin as the trihydrate. Each 5 mL of the 125-mg reconstituted suspension contains 0.11 mEq (2.51 mg) of sodium. Each 5 mL of the 200-mg reconstituted suspension contains 0.15 mEq (3.39 mg) of sodium. Each 5 mL of the 250 mg reconstituted suspension contains 0.15 mEq (3.36 mg) of sodium; each 5 mL of the 400 mg reconstituted suspension contains 0.19 mEq (4.33 mg) of sodium. Inactive ingredients: FD&C Red No. 3, flavorings, silica gel, sodium benzoate, sodium citrate, sucrose, and xanthan gum.

12 CLINICAL PHARMACOLOGY

12.1 Mechanism of Action

Amoxicillin is an antibacterial drug. [see Microbiology (12.4)].

12.3 Pharmacokinetics

Absorption: Amoxicillin is stable in the presence of gastric acid and is rapidly absorbed after oral administration. The effect of food on the absorption of amoxicillin from the tablets and suspension of AMOXICILLIN has been partially investigated; 400-mg and 875-mg formulations have been studied only when administered at the start of a light meal.

Orally administered doses of 250-mg and 500-mg amoxicillin capsules result in average peak blood levels 1 to 2 hours after administration in the range of 3.5 mcg/mL to 5.0 mcg/mL and 5.5 mcg/mL to 7.5 mcg/mL, respectively.

Mean amoxicillin pharmacokinetic parameters from an open, two-part, single-dose crossover bioequivalence study in 27 adults comparing 875 mg of AMOXICILLIN with 875 mg of AUGMENTIN® (amoxicillin/clavulanate potassium) showed that the 875-mg tablet of amoxicillin produces an AUC0-∞ of 35.4 ± 8.1 mcg∙hr/mL and a Cmax of 13.8 ± 4.1 mcg/mL. Dosing was at the start of a light meal following an overnight fast.

Orally administered doses of amoxicillin suspension, 125 mg/5 mL and 250 mg/5 mL, result in average peak blood levels 1 to 2 hours after administration in the range of 1.5 mcg/mL to 3.0 mcg/mL and 3.5 mcg/mL to 5.0 mcg/mL, respectively.

Oral administration of single doses of 400-mg chewable tablets and 400 mg/5 mL suspension of AMOXICILLIN to 24 adult volunteers yielded comparable pharmacokinetic data:

Table 3. Mean Pharmacokinetic Parameters of Amoxicillin (400 mg chewable tablets and 400 mg/5 mL suspension) in Healthy Adults
Dose* | AUC0-∞ (mcg∙hr/mL) | Cmax (mcg/mL)†
Amoxicillin | Amoxicillin (±S.D.) | Amoxicillin (±S.D.)
400 mg (5 mL of suspension) | 17.1 (3.1) | 5.92 (1.62)
400 mg (1 chewable tablet) | 17.9 (2.4) | 5.18 (1.64)

*Administered at the start of a light meal.
†Mean values of 24 normal volunteers. Peak concentrations occurred approximately 1 hour after the dose.

Distribution: Amoxicillin diffuses readily into most body tissues and fluids, with the exception of brain and spinal fluid, except when meninges are inflamed. In blood serum, amoxicillin is approximately 20% protein-bound. Following a 1-gram dose and utilizing a special skin window technique to determine levels of the antibiotic, it was noted that therapeutic levels were found in the interstitial fluid.

Metabolism and Excretion: The half-life of amoxicillin is 61.3 minutes. Approximately 60% of an orally administered dose of amoxicillin is excreted in the urine within 6 to 8 hours. Detectable serum levels are observed up to 8 hours after an orally administered dose of amoxicillin. Since most of the amoxicillin is excreted unchanged in the urine, its excretion can be delayed by concurrent administration of probenecid [see DRUG INTERACTIONS (7.1)].

12.4 Microbiology

Mechanism of Action

Amoxicillin is similar to penicillin in its bactericidal action against susceptible bacteria during the stage of active multiplication. It acts through the inhibition of cell wall biosynthesis that leads to the death of the bacteria.

Method of Resistance

Resistance to amoxicillin is mediated primarily through enzymes called beta-lactamases that cleave the beta-lactam ring of amoxicillin, rendering it inactive.

Amoxicillin has been shown to be active against most isolates of the bacteria listed below, both in vitro and in clinical infections as described in the INDICATIONS AND USAGE section.

Gram-Positive Bacteria

Enterococcus faecalis
Staphylococcus spp.
Streptococcus pneumoniae
Streptococcus spp. (alpha and beta-hemolytic)

Gram-Negative Bacteria
Escherichia coli
Haemophilus influenzae
Helicobacter pylori
Proteus mirabilis

Susceptibility Test Methods:

When available, the clinical microbiology laboratory should provide cumulative in vitro susceptibility test results for antimicrobial drugs used in local hospitals and practice areas to the physician as periodic reports that describe the susceptibility profile of nosocomial and community-acquired pathogens. These reports should aid the physician in selecting the most effective antimicrobial.

Dilution Techniques: Quantitative methods are used to determine antimicrobial minimum inhibitory concentrations (MICs). These MICs provide estimates of the susceptibility of bacteria to antimicrobial compounds. The MICs should be determined using a standardized test method (broth or agar)^2,4. The MIC values should be interpreted according to the criteria in Table 4.

Diffusion Techniques: Quantitative methods that require measurement of zone diameters can also provide reproducible estimates of the susceptibility of bacteria to antimicrobial compounds^3,4. The zone size should be determined using a standardized test method^3.

Susceptibility to amoxicillin of Enterococcus spp., Enterobacteriaceae, and H. influenzae, may be inferred by testing ampicillin^4. Susceptibility to amoxicillin of Staphylococcus spp., and beta-hemolytic Streptococcus spp., may be inferred by testing penicillin^4. The majority of isolates of Enterococcus spp. that are resistant to ampicillin or amoxicillin produce a TEM-type beta-lactamase. A beta-lactamase test can provide a rapid means of determining resistance to ampicillin and amoxicillin^4.

Susceptibility to amoxicillin of Streptococcus pneumoniae (non-meningitis isolates) may be inferred by testing penicillin or oxacillin^4. The interpretive criteria for S. pneumoniae to amoxicillin are provided in Table 4^4.

Table 4. Susceptibility Test Interpretive Criteria for Amoxicillin
 | Minimum Inhibitory Concentration (mcg/mL) |  |  | Disk Diffusion (zone diameter in mm)
 | Susceptible | Intermediate | Resistant | Susceptible | Intermediate | Resistant
Streptococcus pneumoniae (non-meningitis isolates)* | ≤ 2 | 4 | ≥ 8 | - | - | -

* S. pneumoniae should be tested using a 1-mcg oxacillin disk. Isolates with oxacillin zone sizes of ≥ 20 mm are susceptible to amoxicillin. An amoxicillin MIC should be determined on isolates of S. pneumoniae with oxacillin zone sizes of ≤ 19 mm^4.

A report of “Susceptible” indicates the antimicrobial is likely to inhibit growth of the pathogen if the antimicrobial compound reaches a concentration at the infection site necessary to inhibit growth of the pathogen. A report of “Intermediate” indicates that the result should be considered equivocal, and, if the microorganism is not fully susceptible to alternative, clinically feasible drugs, the test should be repeated. This category implies possible clinical applicability in body sites where the drug is physiologically concentrated. This category also provides a buffer zone that prevents small uncontrolled technical factors from causing major discrepancies in interpretation. A report of “Resistant” indicates the antimicrobial is not likely to inhibit growth of the pathogen if the antimicrobial compound reaches the concentration usually achievable at the infection site; other therapy should be selected.

Susceptibility Testing for Helicobacter pylori

Amoxicillin in vitro susceptibility testing methods for determining minimum inhibitory concentrations (MICs) and zone sizes have not been standardized, validated, or approved for testing H. pylori. Specimens for H. pylori and clarithromycin susceptibility test results should be obtained on isolates from patients who fail triple therapy. If clarithromycin resistance is found, a non-clarithromycin-containing regimen should be used.

Quality Control:

Standardized susceptibility test procedures ^2,3,4 require use of laboratory controls to monitor and ensure the accuracy and precision of the supplies and reagents used in the assay, and the techniques of the individuals performing the test control. Standard amoxicillin powder should provide the following range of MIC values provided in Table 5^4. For the diffusion technique the criteria provided in Table 5 should be achieved.

Table 5. Acceptable Quality Control Ranges for Amoxicillina
Quality Control Microorganism |  | Minimum Inhibitory Concentrations (mcg/mL) | Disc Diffusion Zone Diameter (mm)
Streptococcus pneumoniae ATCCb 49619 |  | 0.03 to 0.12 | --
Klebsiella pneumoniae ATCC 700603 |  | >128 | --

a QC limits for testing E. coli 35218 when tested on Haemophilus Test Medium (HTM) are ≥ 256 mcg/mL for amoxicillin; testing amoxicillin may help to determine if the isolate has maintained its ability to produce beta-lactamase^4.
b ATCC = American Type Culture Collection

13 NONCLINICAL TOXICOLOGY

13.1 Carcinogenesis, Mutagenesis, Impairment of Fertility

Long-term studies in animals have not been performed to evaluate carcinogenic potential. Studies to detect mutagenic potential of amoxicillin alone have not been conducted; however, the following information is available from tests on a 4:1 mixture of amoxicillin and potassium clavulanate (AUGMENTIN). AUGMENTIN was non-mutagenic in the Ames bacterial mutation assay, and the yeast gene conversion assay. AUGMENTIN was weakly positive in the mouse lymphoma assay, but the trend toward increased mutation frequencies in this assay occurred at doses that were also associated with decreased cell survival. AUGMENTIN was negative in the mouse micronucleus test and in the dominant lethal assay in mice. Potassium clavulanate alone was tested in the Ames bacterial mutation assay and in the mouse micronucleus test, and was negative in each of these assays. In a multi-generation reproduction study in rats, no impairment of fertility or other adverse reproductive effects were seen at doses up to 500 mg/kg (approximately 2 times the 3 g human dose based on body surface area).

14 CLINICAL STUDIES

14.1 H. pylori Eradication to Reduce the Risk of Duodenal Ulcer Recurrence

Randomized, double-blind clinical studies performed in the United States in patients with H. pylori and duodenal ulcer disease (defined as an active ulcer or history of an ulcer within 1 year) evaluated the efficacy of lansoprazole in combination with amoxicillin capsules and clarithromycin tablets as triple 14-day therapy, or in combination with amoxicillin capsules as dual 14-day therapy, for the eradication of H. pylori. Based on the results of these studies, the safety and efficacy of 2 different eradication regimens were established: Triple therapy: Amoxicillin 1 gram twice daily/clarithromycin 500 mg twice daily/lansoprazole 30 mg twice daily (see Table 6). Dual therapy: Amoxicillin 1 gram three times daily/lansoprazole 30 mg three times daily (see Table 7). All treatments were for 14 days. H. pylori eradication was defined as 2 negative tests (culture and histology) at 4 to 6 weeks following the end of treatment. Triple therapy was shown to be more effective than all possible dual therapy combinations. Dual therapy was shown to be more effective than both monotherapies. Eradication of H. pylori has been shown to reduce the risk of duodenal ulcer recurrence.

Table 6. H. pylori Eradication Rates When Amoxicillin is Administered as Part of a Triple Therapy Regimen
Study | Triple Therapy | Triple Therapy
Study |  | Evaluable Analysis a [95% Confidence Interval] (number of patients) | Intent-to-Treat Analysisb [95% Confidence Interval] (number of patients)
Study 1 | 92 [80.0 - 97.7] (n = 48) | 86 [73.3 - 93.5] (n = 55)
Study 2 | 86 [75.7 - 93.6] (n = 66) | 83 [72.0 - 90.8] (n = 70)

a This analysis was based on evaluable patients with confirmed duodenal ulcer (active or within 1 year) and H. pylori infection at baseline defined as at least 2 of 3 positive endoscopic tests from CLOtest®, histology, and/or culture. Patients were included in the analysis if they completed the study. Additionally, if patients dropped out of the study due to an adverse event related to the study drug, they were included in the analysis as failures of therapy.
b Patients were included in the analysis if they had documented H. pylori infection at baseline as defined above and had a confirmed duodenal ulcer (active or within 1 year). All dropouts were included as failures of therapy.

Table 7. H. pylori Eradication Rates When Amoxicillin is Administered as Part of a Dual Therapy Regimen
Study | Dual Therapy | Dual Therapy
Study |  | Evaluable Analysisa [95% Confidence Interval] (number of patients) | Intent-to-Treat Analysisb [95% Confidence Interval] (number of patients)
Study 1 | 77 [62.5 - 87.2] (n = 51) | 70 [56.8 - 81.2] (n = 60)
Study 2 | 66 [51.9 - 77.5] (n = 58) | 61 [48.5 - 72.9] (n = 67)

a This analysis was based on evaluable patients with confirmed duodenal ulcer (active or within 1 year) and H. pylori infection at baseline defined as at least 2 of 3 positive endoscopic tests from CLOtest®, histology, and/or culture. Patients were included in the analysis if they completed the study. Additionally, if patients dropped out of the study due to an adverse event related to the study drug, they were included in the analysis as failures of therapy.
b Patients were included in the analysis if they had documented H. pylori infection at baseline as defined above and had a confirmed duodenal ulcer (active or within 1 year). All dropouts were included as failures of therapy.

15 REFERENCES

1. Swanson-Biearman B, Dean BS, Lopez G, Krenzelok EP. The effects of penicillin and cephalosporin ingestions in children less than six years of age. Vet Hum Toxicol. 1988; 30: 66 67.
2. Clinical and Laboratory Standards Institute (CLSI). Methods for Dilution Antimicrobial Susceptibility Tests for Bacteria that Grow Aerobically; Approved Standard – Tenth Edition. CLSI document M07-A10, Clinical and Laboratory Standards Institute, 950 West Valley Road, Suite 2500, Wayne, Pennsylvania 19087, USA, 2015.
3. Clinical and Laboratory Standards Institute (CLSI). Performance Standards for Antimicrobial Disk Diffusion Susceptibility Tests; Approved Standard – Twelfth Edition. CLSI document M02-A12, Clinical and Laboratory Standards Institute, 950 West Valley Road, Suite 2500, Wayne, Pennsylvania 19087, USA, 2015.
4. Clinical and Laboratory Standards Institute (CLSI). Performance Standards for Antimicrobial Susceptibility Testing; Twenty-fifth Informational Supplement, CLSI document M100-S25. CLSI document M100-S25, Clinical and Laboratory Standards Institute, 950 West Valley Road, Suite 2500, Wayne, Pennsylvania 19087, USA, 2015.

16 HOW SUPPLIED/STORAGE AND HANDLING

Product: 50436-4543

NDC: 50436-4543-1 20 TABLET, FILM COATED in a BOTTLE

17 PATIENT COUNSELING INFORMATION

Information for Patients

- Patients should be advised that AMOXICILLIN may be taken every 8 hours or every 12 hours, depending on the dose prescribed.
- Patients should be counseled that antibacterial drugs, including AMOXICILLIN, should only be used to treat bacterial infections. They do not treat viral infections (e.g., the common cold). When AMOXICILLIN is prescribed to treat a bacterial infection, patients should be told that although it is common to feel better early in the course of therapy, the medication should be taken exactly as directed. Skipping doses or not completing the full course of therapy may: (1) decrease the effectiveness of the immediate treatment, and (2) increase the likelihood that bacteria will develop resistance and will not be treatable by AMOXICILLIN or other antibacterial drugs in the future.
- Patients should be counseled that diarrhea is a common problem caused by antibiotics, and it usually ends when the antibiotic is discontinued. Sometimes after starting treatment with antibiotics, patients can develop watery and bloody stools (with or without stomach cramps and fever) even as late as 2 or more months after having taken their last dose of the antibiotic. If this occurs, patients should contact their physician as soon as possible.
- Patients should be aware that AMOXICILLIN contains a penicillin class drug product that can cause allergic reactions in some individuals.

AMOXIL is registered trademark of GlaxoSmithKline and is licensed to Dr. Reddy’s Laboratories Inc.

Manufactured. By:
Dr. Reddy’s Laboratories Tennessee LLC.
Bristol, TN 37620

Issued: 072016